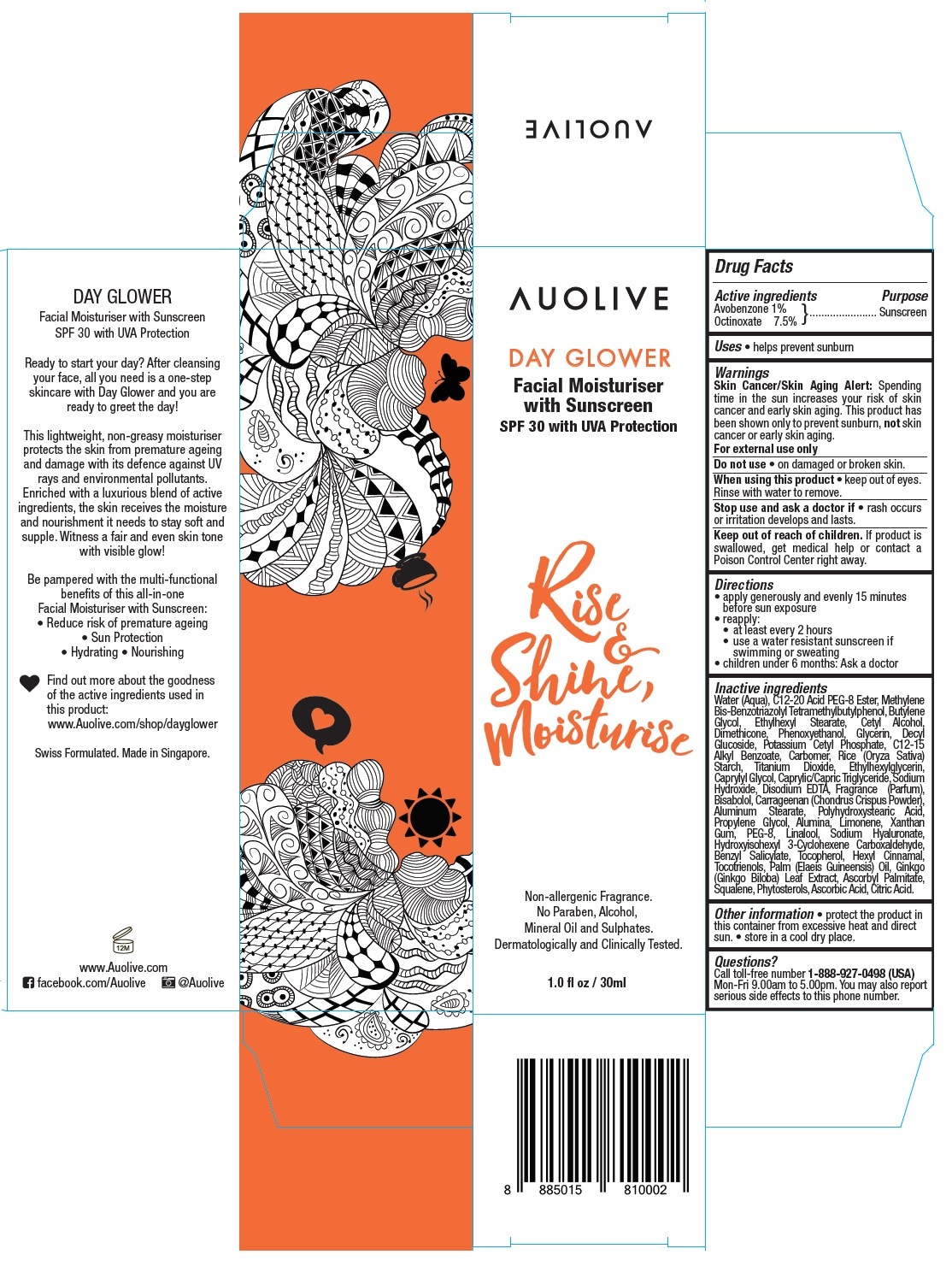 DRUG LABEL: Auolive Day Glower Facial Moisturiser with Sunscreen
NDC: 71191-101 | Form: CREAM
Manufacturer: Skin Balance Pte. Ltd.
Category: otc | Type: HUMAN OTC DRUG LABEL
Date: 20170221

ACTIVE INGREDIENTS: AVOBENZONE 1 g/100 mL; OCTINOXATE 7.5 g/100 mL
INACTIVE INGREDIENTS: WATER; C12-20 ACID PEG-8 ESTER; BISOCTRIZOLE; BUTYLENE GLYCOL; ETHYLHEXYL STEARATE; CETYL ALCOHOL; DIMETHICONE; PHENOXYETHANOL; GLYCERIN; DECYL GLUCOSIDE; POTASSIUM CETYL PHOSPHATE; ALKYL (C12-15) BENZOATE; CARBOXYPOLYMETHYLENE; STARCH, RICE; TITANIUM DIOXIDE; ETHYLHEXYLGLYCERIN; CAPRYLYL GLYCOL; MEDIUM-CHAIN TRIGLYCERIDES; SODIUM HYDROXIDE; EDETATE DISODIUM ANHYDROUS; LEVOMENOL; CARRAGEENAN; ALUMINUM STEARATE; POLYHYDROXYSTEARIC ACID (2300 MW); PROPYLENE GLYCOL; ALUMINUM OXIDE; LIMONENE, (+)-; XANTHAN GUM; POLYETHYLENE GLYCOL 400; LINALOOL, (+/-)-; HYALURONATE SODIUM; HYDROXYISOHEXYL 3-CYCLOHEXENE CARBOXALDEHYDE; BENZYL SALICYLATE; TOCOPHEROL; .ALPHA.-HEXYLCINNAMALDEHYDE; TOCOTRIENOLS; PALM OIL; GINKGO; ASCORBYL PALMITATE; SQUALENE; PHYTOSTERYL MACADAMIATE; ASCORBIC ACID; CITRIC ACID MONOHYDRATE

Auolive Day Glower Facial Moisturiser with Sunscreen

Active ingredients

Avobenzone 1%
Octinoxate 7.5%

Purpose

Sunscreen

Uses

• helps prevent sunburn

Warnings

Skin Cancer/Skin Aging Alert: Spending time in the sun increases your risk of skin cancer and early skin aging. This product has been shown only to prevent sunburn, not skin cancer or early skin aging.
For external use only
Do not use ● on damaged or broken skin.
When using this product ● keep out of eyes. Rinse with water to remove.
Stop use and ask a doctor if ● rash occurs or irritation develops and lasts.

Keep out of reach of children. If product is swallowed, get medical help or contact a Poison Control Center right away.

Directions

• apply generously and evenly 15 minutes before sun exposure
• reapply:
• at least every 2 hours
• use a water resistant sunscreen if swimming or sweating
• children under 6 months: Ask a doctor

Inactive ingredients

Water (Aqua), C12-20 Acid PEG-8 Ester, Methylene Bis-Benzotriazolyl Tetramethylbutylphenol, Butylene Glycol, Ethylhexyl Stearate, Cetyl Alcohol, Dimethicone, Phenoxyethanol, Glycerin, Decyl Glucoside, Potassium Cetyl Phosphate, C12-15 Alkyl Benzoate, Carbomer, Rice (Oryza Sativa) Starch, Titanium Dioxide, Ethylhexylglycerin, Caprylyl Glycol, Caprylic/Capric Triglyceride, Sodium Hydroxide, Disodium EDTA, Fragrance (Parfum), Bisabolol, Carrageenan (Chondrus Crispus Powder), Aluminum Stearate, Polyhydroxystearic Acid, Propylene Glycol, Alumina, Limonene, Xanthan Gum, PEG-8, Linalool, Sodium Hyaluronate, Hydroxyisohexyl 3-Cyclohexene Carboxaldehyde, Benzyl Salicylate, Tocopherol, Hexyl Cinnamal, Tocotrienols, Palm (Elaeis Guineensis) Oil, Ginkgo (Ginkgo Biloba) Leaf Extract, Ascorbyl Palmitate, Squalene, Phytosterols, Ascorbic Acid, Citric Acid.

Other information

- protect the product in this container from excessive heat and direct sun.
- store in a cool dry place.

Questions?

Call toll-free number 1-888-927-0498 (USA)
Mon-Fri 9.00am to 5.00pm. You may also report serious side effects to this phone number.

SPF 30 with UVA Protection

Rise & Shine, Moisturise

Non-allergenic Fragrance.
No Paraben, Alcohol, Mineral Oil and Sulphates.
Dermatologically and Clinically Tested.

Ready to start your day? After cleansing your face, all you need is a one-step skincare with Day Glower and you are ready to greet the day!

This lightweight, non-greasy moisturiser protects the skin from premature ageing and damage with its defence against UV rays and environmental pollutants.

Enriched with a luxurious blend of active ingredients, the skin receives the moisture and nourishment it needs to stay soft and supple. Witness a fair and even skin tone with visible glow!

Be pampered with the multi-functional benefits of this all-in-one Facial Moisturiser with Sunscreen:
• Reduce risk of premature ageing
• Sun Protection
• Hydrating
• Nourishing

Find out more about the goodness of the active ingredients used in this product:
www.Auolive.com/shop/dayglower

Swiss Formulated. Made in Singapore.